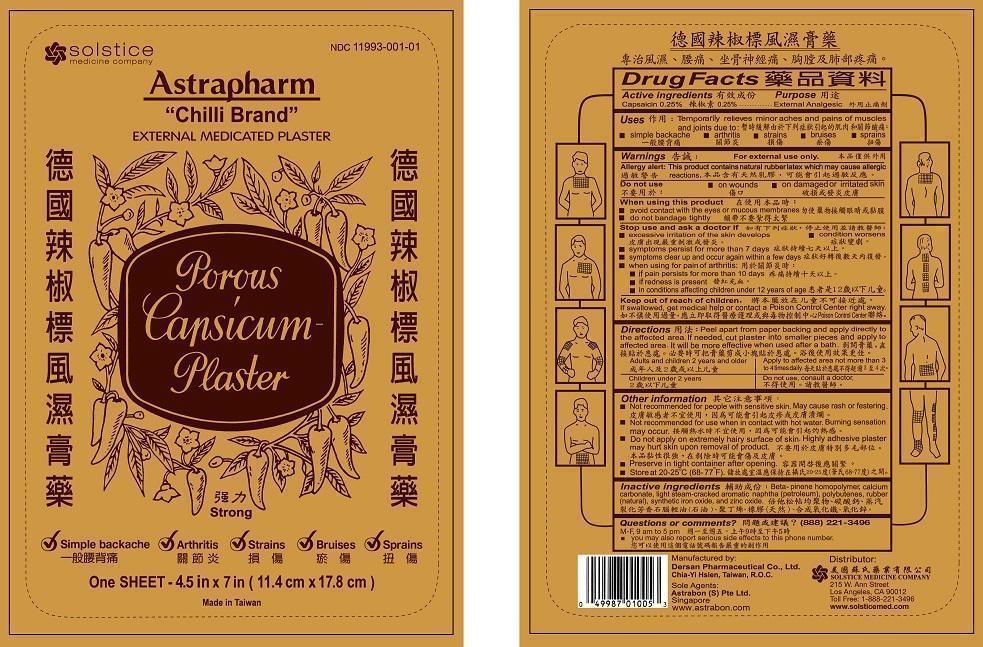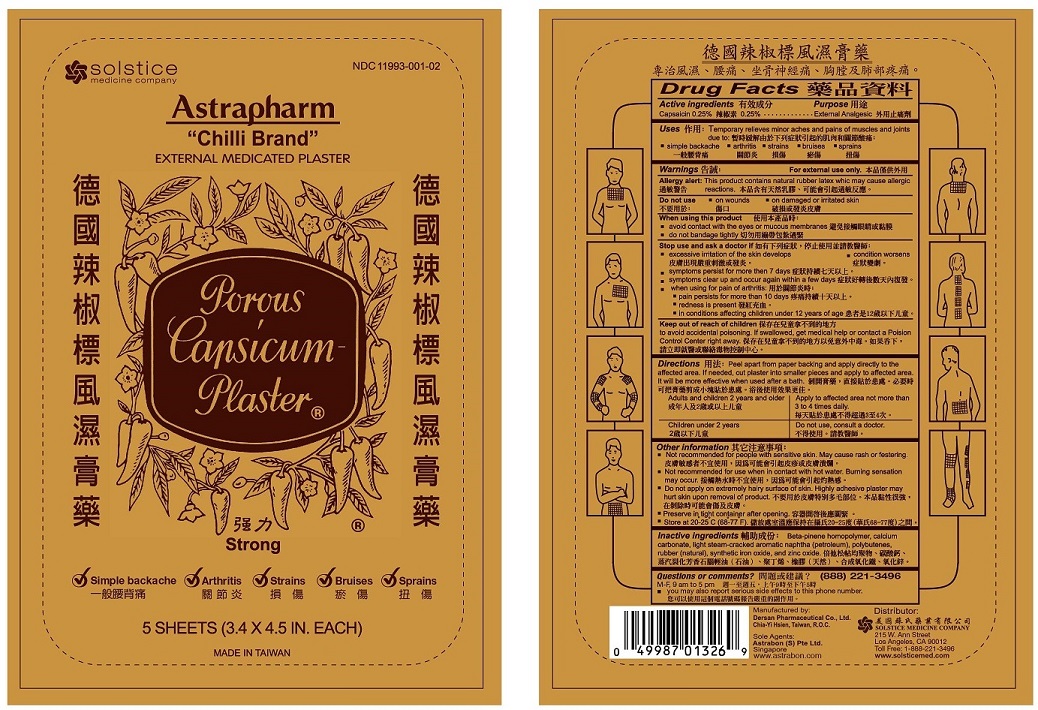 DRUG LABEL: ASTRAPHARM CHILLI BRAND EXTERNAL MEDICATED
NDC: 11993-001 | Form: PLASTER
Manufacturer: DERSAN PHARMACEUTICAL CO LTD
Category: otc | Type: HUMAN OTC DRUG LABEL
Date: 20170601

ACTIVE INGREDIENTS: CAPSAICIN 70 mg/1 1
INACTIVE INGREDIENTS: .BETA.-PINENE; CALCIUM CARBONATE; NAPHTHA; POLYBUTENE (1400 MW); NATURAL LATEX RUBBER; FERRIC OXIDE RED; ZINC OXIDE

DRUG FACTS

Active ingredients
Capsaicin 0.25%

Purpose
External analgesic

INDICATIONS AND USAGE

Uses Temporarily relieves minor aches and pains of muscles and joints due to:

- simple backache
- arthritis
- strains
- bruises
- sprains

Warnings
For external use only
Allergy alert: This product contains natural rubber latex which may cause allergic reactions

Do not use

- on wounds
- on irritated or damaged skin

When using this product

- avoid contact with the eyes or mucous membranes
- do not bandage tightly

Stop use and ask a doctor if

- excessive irritation of the skin develops
- condition worsens
- symptoms persist for more than 7 days
- symptoms clear up and occur again within a few days
- when using for pain of arthritis:
  - if pain persists for more than 10 days
  - if redness is present
  - in conditions affecting children under 12 years of age

Keep out of reach of children. If swallowed, get medical help or contact a Poison Control Center right away.

Directions

- Peel apart from paper backing and apply directly to the affected area. If needed, cut plaster into small pieces and apply to affected area. It will be more effective when used after a bath.
- Adults and children 2 years and older: Apply to affected area no more than 3 to 4 times daily.
- Children under 2 years: Do not use, consult a doctor.

Other information

- Not recommended for people with sensitive skin. May cause rash or festering.
- Not recommended for use when in contact with hot water. Burning sensation may occur.
- Do not apply on extremely hairy surface of skin. Highly adhesive plaster may hurt skin upon removal of product.
- Preserve in tight container after opening.
- Store at 20-25°C (68-77°F)

INACTIVE INGREDIENT

Inactive ingredients Beta-pinene homopolymer, calcium carbonate, light steam-cracked aromatic naphtha (petroleum), polybutenes, rubber (natural), synthetic iron oxide, and zinc oxide.

Questions or comments? (888) 221-3496 M-F 9 am to 5 pm

- you may also report serious side effects to this phone number

PACKAGE LABEL

ASTRAPHARM CHILLI BRAND EXTERNAL MEDICATED PLASTER
NDC 11993-001-01
Simple backache, Arthritis, Strains, Bruises, Sprains
1 Sheet - 4.5 in x 7 in (11.4 cm x 17.8 cm)

PACKAGE LABEL

ASTRAPHARM CHILLI BRAND EXTERNAL MEDICATED PLASTER
NDC 11993-001-02
Simple backache, Arthritis, Strains, Bruises, Sprains
5 Sheets - (3.4 x 4.5 in Each)